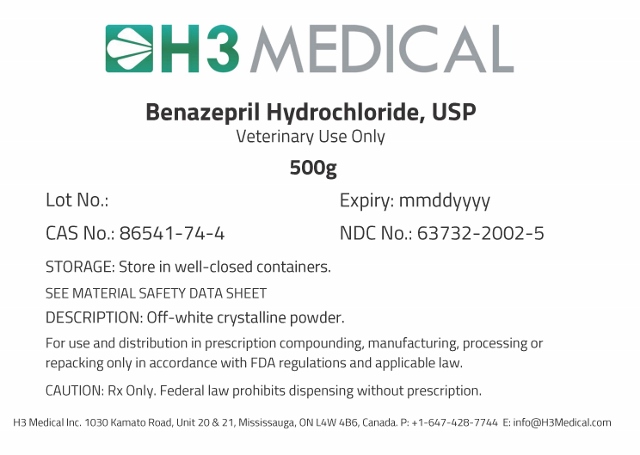 DRUG LABEL: Benazepril Hydrochloride
NDC: 63732-2002 | Form: POWDER
Manufacturer: H3 MEDICAL INC.
Category: other | Type: BULK INGREDIENT
Date: 20181220

ACTIVE INGREDIENTS: BENAZEPRIL HYDROCHLORIDE 1 g/1 g

Benazepril Hydrochloride